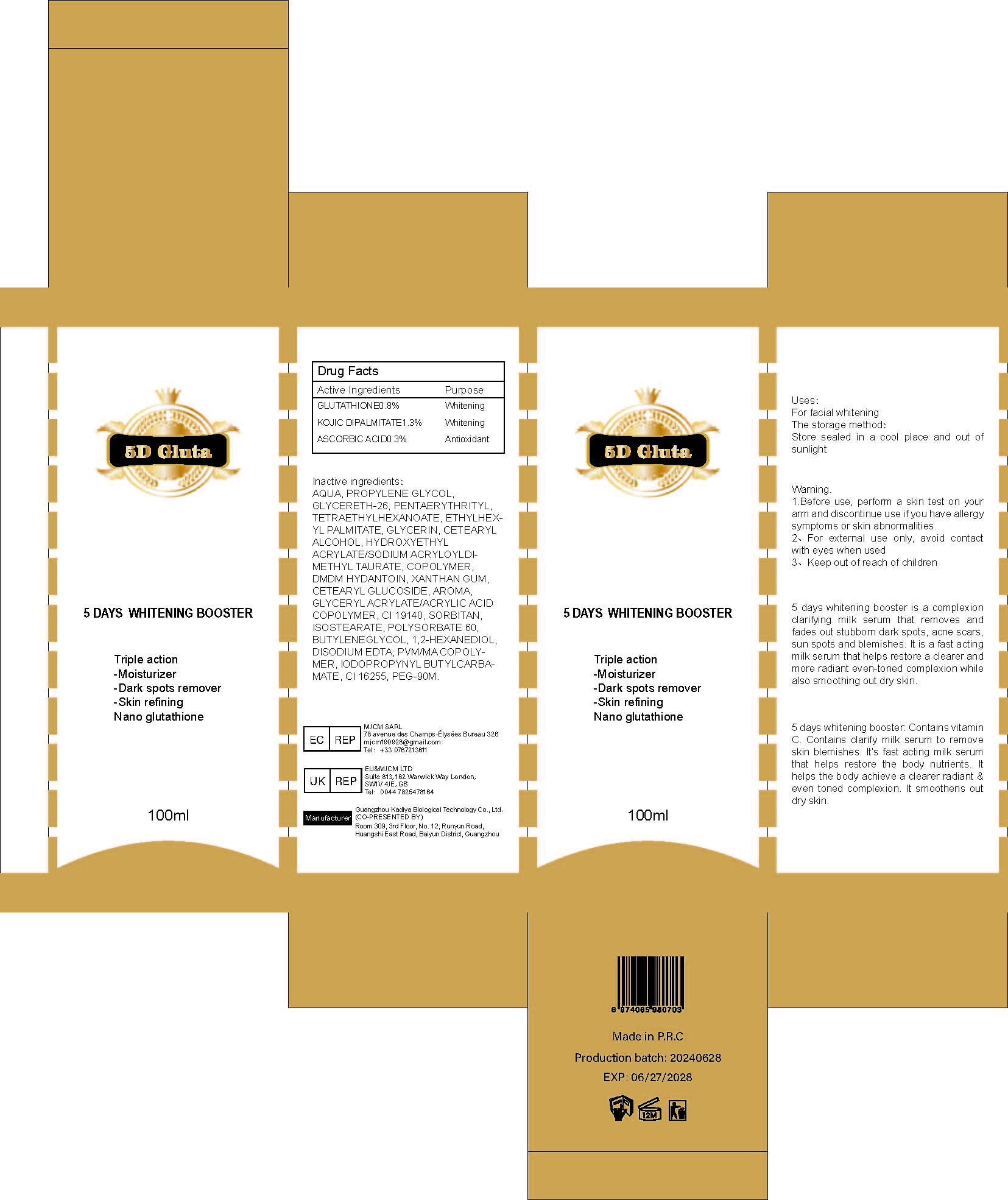 DRUG LABEL: 5 DAYS WHITENING BOOSTER
NDC: 84423-017 | Form: LIQUID
Manufacturer: Guangzhou Kadiya Biotechnology Co., Ltd.
Category: otc | Type: HUMAN OTC DRUG LABEL
Date: 20240709

ACTIVE INGREDIENTS: GLUTATHIONE 0.8 mg/100 mg; KOJIC DIPALMITATE 1.3 mg/100 mg; ASCORBIC ACID 0.3 mg/100 mg
INACTIVE INGREDIENTS: CETOSTEARYL ALCOHOL; HYDROXYETHYL ACRYLATE/SODIUM ACRYLOYLDIMETHYL TAURATE COPOLYMER (45000 MPA.S AT 1%); EDETATE DISODIUM; WATER; GLYCERETH-26; XANTHAN GUM; CETEARYL GLUCOSIDE; 1,4-BUTANEDIOL; FD&C YELLOW NO. 5; 1,2-HEXANEDIOL; DMDM HYDANTOIN; GLYCERYL ACRYLATE/ACRYLIC ACID COPOLYMER (300000 CP AT 2%); POLYSORBATE 60; IODOPROPYNYL BUTYLCARBAMATE; PONCEAU 4R; POLYETHYLENE GLYCOL 4000000; PENTAERYTHRITYL TETRAETHYLHEXANOATE; ETHYLHEXYL PALMITATE; GLYCERIN; PROPYLENE GLYCOL; SORBITAN ISOSTEARATE; METHYL VINYL ETHER AND MALEIC ANHYDRIDE COPOLYMER (1100000 WAMW)

Uses：
For facial whitening

INACTIVE INGREDIENT

AQUA、PROPYLENE GLYCOL、GLYCERETH-26、PENTAERYTHRITYL、TETRAETHYLHEXANOATE、ETHYLHEXYL PALMITATE、GLYCERIN、CETEARYL ALCOHOL、HYDROXYETHYL ACRYLATE/SODIUM ACRYLOYLDIMETHYL TAURATE、COPOLYMER、DMDM HYDANTOIN、XANTHAN GUM、CETEARYL GLUCOSIDE、AROMA、GLYCERYL ACRYLATE/ACRYLIC ACID COPOLYMER、CI 19140、SORBITAN、ISOSTEARATE、POLYSORBATE 60、BUTYLENEGLYCOL、1,2-HEXANEDIOL、DISODIUM EDTA、PVM/MA COPOLYMER、IODOPROPYNYL BUTYLCARBAMATE、CI 16255、PEG-90M

Warning.
1.Before use, perform a skin test on your arm and discontinue use if you have allergy symptoms or skin abnormalities.
2、For external use only, avoid contact with eyes when used
3、Keep out of reach of children

INDICATIONS AND USAGE

Triple action
-Moisturizer
-Dark spots remover
-Skin refining
Nano glutathione

KEEP OUT OF REACH OF CHILDREN SECTION

Active Ingredients
GLUTATHIONE 0.8%
KOJIC DIPALMITATE 1.3%
ASCORBIC ACID 0.3%

DOSAGE AND ADMINISTRATION

a complexion
clarifying milk serum that removes and
fades out stubborn dark spots, acne scars,
sun spots and blemishes. It is a fast acting
milk serum that helps restore a clearer and
more radiant even-toned complexion while
also smoothing out dry skin.

PACKAGE LABEL

Active Ingredients
GLUTATHIONE 0.8%
KOJIC DIPALMITATE 1.3%
ASCORBIC ACID 0.3%

Uses：
For facial whitening
Indications: For facial whitening
The storage method：
Store sealed in a cool place and out of sunlight

Warning.
1.Before use, perform a skin test on your arm and discontinue use if you have allergy symptoms or skin abnormalities.
2、For external use only, avoid contact with eyes when used
3、Keep out of reach of children

Inactive ingredients：
AQUA、PROPYLENE GLYCOL、GLYCERETH-26、PENTAERYTHRITYL、TETRAETHYLHEXANOATE、ETHYLHEXYL PALMITATE、GLYCERIN、CETEARYL ALCOHOL、HYDROXYETHYL ACRYLATE/SODIUM ACRYLOYLDIMETHYL TAURATE、COPOLYMER、DMDM HYDANTOIN、XANTHAN GUM、CETEARYL GLUCOSIDE、AROMA、GLYCERYL ACRYLATE/ACRYLIC ACID COPOLYMER、CI 19140、SORBITAN、ISOSTEARATE、POLYSORBATE 60、BUTYLENEGLYCOL、1,2-HEXANEDIOL、DISODIUM EDTA、PVM/MA COPOLYMER、IODOPROPYNYL BUTYLCARBAMATE、CI 16255、PEG-90M